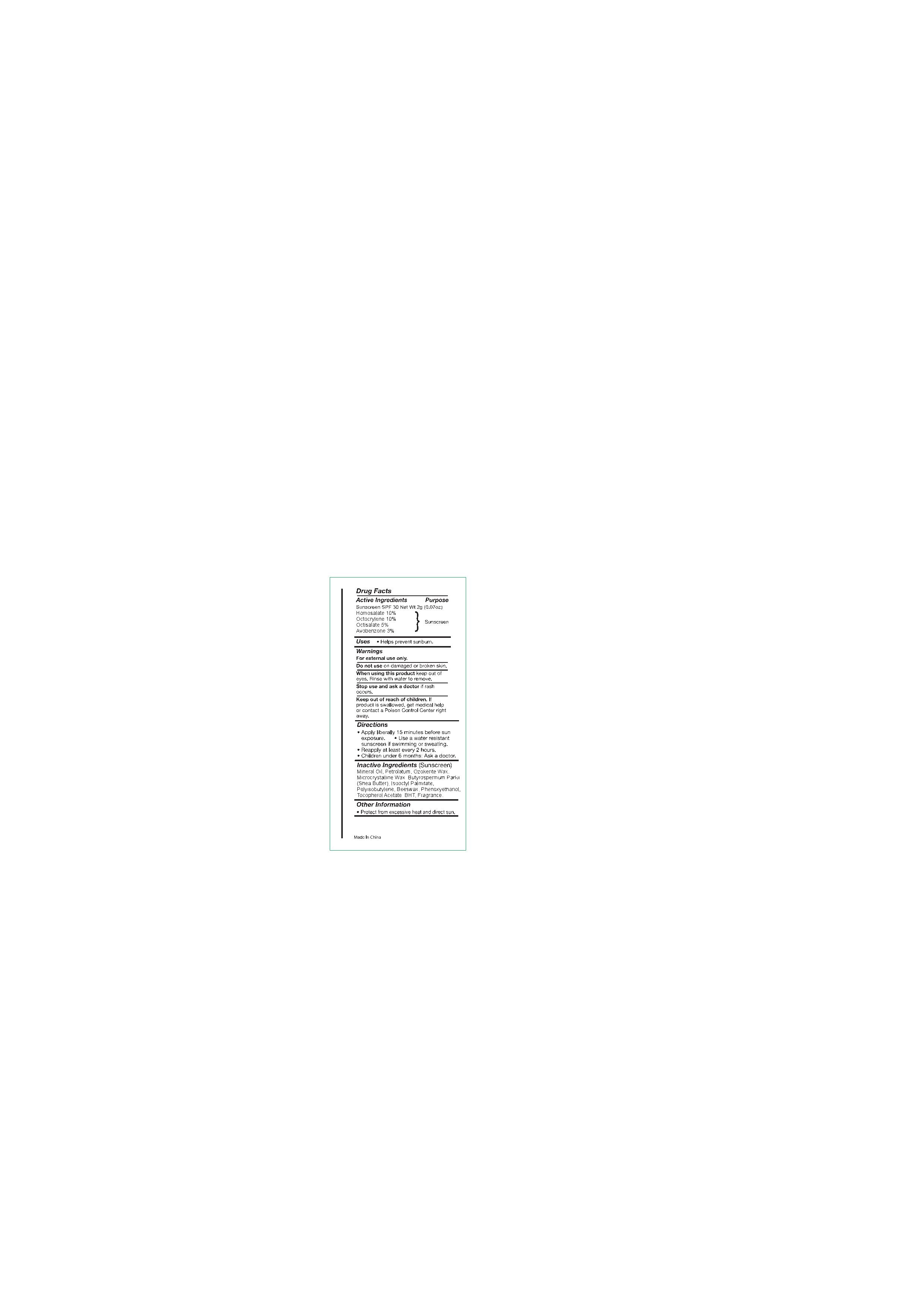 DRUG LABEL: Sunscreen Stick SPF30( CB400)
NDC: 82953-043 | Form: LIPSTICK
Manufacturer: Cosmuses Cosmetics (Ningbo) Co., Ltd.
Category: otc | Type: HUMAN OTC DRUG LABEL
Date: 20250328

ACTIVE INGREDIENTS: OCTOCRYLENE 10 g/100 g; HOMOSALATE 10 g/100 g; AVOBENZONE 3 g/100 g; OCTISALATE 5 g/100 g
INACTIVE INGREDIENTS: BHT; MINERAL OIL; BEESWAX; CERESIN; PHENOXYETHANOL; OCTYL PALMITATE; FRAGRANCE 13576; MICROCRYSTALLINE WAX; POLYISOBUTYLENE (1000 MW); BUTYROSPERMUM PARKII (SHEA) BUTTER; .ALPHA.-TOCOPHEROL ACETATE, DL-; PETROLATUM

Sunscreen Stick SPF30 (CB400)

Drug Facts

Active ingredients

Homosalate 10%

Octocrylene 10%

Octisalate 5%

Avobenzone 3%

Purpose

Sunscreen

Uses

- Helps prevent sunburn

warnings

For external use only.

Do not use on damaged or broken skin.

when using this product keep out of eyes, rinse with water to remove.

Stop use and ask a doctor if rash occurs.

Keep out of reach of children. If product is swallowed, get medical help or contact a Poison Control Center right away.

Directions

- Apply liberally 15minutes before sun exposure
- Use a water resistant sunscreen if swimming or sweating.
- Reapply at least every 2 hours.
- Children under 6 months of age: Ask a doctor.

Inactive ingredients

Mineral Oil, Petrolatum, Ozokerite wax, Microcrystalline wax, Butyrospermum Parkii (Shea) Butter, Isooctyl palmitate, Polyisobutene, Beeswax, Phenoxyethanol, Tocopherol acetate, BHT, Fragrance

other information

protect form excessive heat and direct sun.